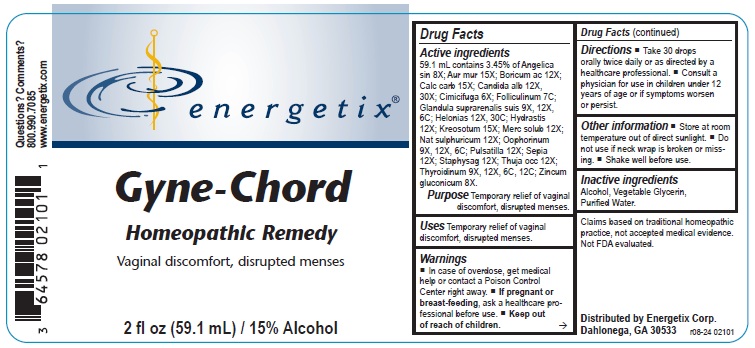 DRUG LABEL: Gyne-Chord
NDC: 64578-0063 | Form: LIQUID
Manufacturer: Energetix Corporation
Category: homeopathic | Type: HUMAN OTC DRUG LABEL
Date: 20241211

ACTIVE INGREDIENTS: ANGELICA SINENSIS ROOT 8 [hp_X]/59.1 mL; GOLD TRICHLORIDE 15 [hp_X]/59.1 mL; BORIC ACID 12 [hp_X]/59.1 mL; OYSTER SHELL CALCIUM CARBONATE, CRUDE 15 [hp_X]/59.1 mL; CANDIDA ALBICANS 12 [hp_X]/59.1 mL; BLACK COHOSH 6 [hp_X]/59.1 mL; ESTRONE 7 [hp_C]/59.1 mL; SUS SCROFA ADRENAL GLAND 9 [hp_X]/59.1 mL; CHAMAELIRIUM LUTEUM ROOT 12 [hp_X]/59.1 mL; GOLDENSEAL 12 [hp_X]/59.1 mL; WOOD CREOSOTE 15 [hp_X]/59.1 mL; MERCURIUS SOLUBILIS 12 [hp_X]/59.1 mL; SODIUM SULFATE 12 [hp_X]/59.1 mL; SUS SCROFA OVARY 9 [hp_X]/59.1 mL; PULSATILLA VULGARIS 12 [hp_X]/59.1 mL; SEPIA OFFICINALIS JUICE 12 [hp_X]/59.1 mL; DELPHINIUM STAPHISAGRIA SEED 12 [hp_X]/59.1 mL; THUJA OCCIDENTALIS LEAFY TWIG 12 [hp_X]/59.1 mL; THYROID, UNSPECIFIED 9 [hp_X]/59.1 mL; ZINC GLUCONATE 8 [hp_X]/59.1 mL
INACTIVE INGREDIENTS: WATER; GLYCERIN; ALCOHOL

Gyne-Chord

ACTIVE INGREDIENT

Active ingredients59.1 mL contains 3.45% of: Angelica sin 8X; Aur mur 15X; Boricum ac 12X; Calc carb 15X; Candida alb 12X, 30X; Cimicifuga 6X; Folliculinum 7C; Glandula suprarenalis suis 9X, 12X, 6C; Helonias 12X, 30C; Hydrastis 12X; Kreosotum 15X; Merc solub 12X; Nat sulphuricum 12X; Oophorinum 9X, 12X, 6C; Pulsatilla 12X; Sepia 12X; Staphysag 12X; Thuja occ 12X; Thyroidinum 9X, 12X, 6C, 12C; Zincum gluconicum 8X.

Claims based on traditional homeopathic practice, not accepted medical evidence. Not FDA evaluated.

Uses

Temporary relief of vaginal discomfort, disrupted menses.

Warnings

- In case of overdose, get medical help or contact a Poison Control Center right away.
- If pregnant or breast-feeding, ask a healthcare professional before use.

• Keep out of reach of children.

Directions

- Take 30 drops orally twice daily or as directed by a healthcare professional.
- Consult a physician for use in children under 12 years of age or if symptoms worsen or persist.

Other information

- Store at room temperature out of direct sunlight.
- Do not use if neck wrap is broken or missing.
- Shake well before use.

Inactive ingredientsAlcohol, Vegetable Glycerin, Purified Water.

QUESTIONS

Distributed by Energetix Corp.

Dahlonega, GA 30533

Questions? Comments?

800.990.7085

www.energetix.com

PACKAGE LABEL

energetix®

Gyne-Chord

Homeopathic Remedy

Vaginal discomfort, disrupted menses.

2 fl oz (59.1 mL) / 15% Alcohol

Purpose Temporary relief of vaginal discomfort, disrupted menses.